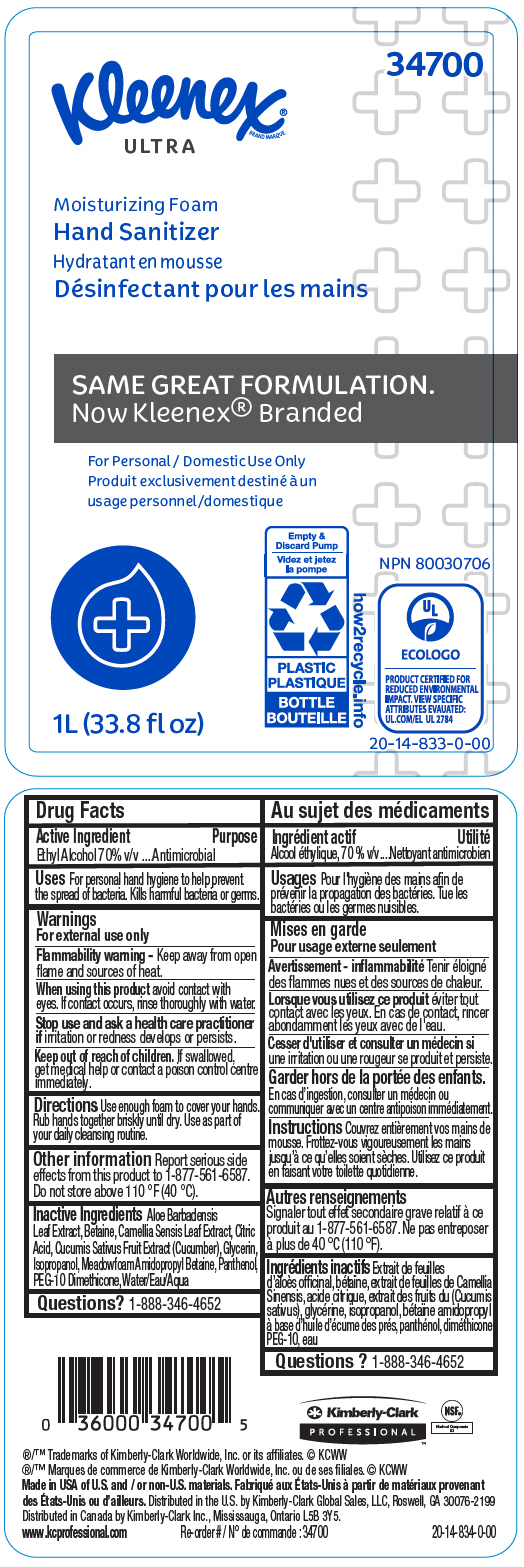 DRUG LABEL: Kleenex Ultra Moisturizing Hand Sanitizer
NDC: 55118-530 | Form: SOLUTION
Manufacturer: Kimberly-Clark Corporation
Category: otc | Type: HUMAN OTC DRUG LABEL
Date: 20241210

ACTIVE INGREDIENTS: Alcohol 70 mL/100 mL
INACTIVE INGREDIENTS: Water; Isopropyl Alcohol; Betaine; CITRIC ACID MONOHYDRATE; GREEN TEA LEAF; Panthenol; Glycerin; MEADOWFOAMAMIDOPROPYL BETAINE; Aloe Vera Leaf; Cucumber

Kleenex® ULTRA Moisturizing Foam Hand Sanitizer

Drug Facts

Active Ingredient

Ethyl Alcohol 70% v/v

Purpose

Antimicrobial

Uses

For personal hand hygiene to help prevent the spread of bacteria. Kills harmful bacteria or germs.

Warnings

For external use only

Flammability warning

Keep away from open flame and sources of heat.

When using this product avoid contact with eyes. If contact occurs, rinse thoroughly with water.

Stop use and ask a health care practitioner if irritation or redness develops or persists.

Keep out of reach of children. If swallowed, get medical help or contact a poison control centre immediately.

Directions

Use enough foam to cover your hands. Rub hands together briskly until dry. Use as part of your daily cleansing routine.

Other information

Report serious side effects from this product to 1-877-561-6587.

Do not store above 110 °F (40 °C).

Inactive Ingredients

Aloe Barbadensis Leaf Extract, Betaine, Camellia Sensis Leaf Extract, Citric Acid, Cucumis Sativus Fruit Extract (Cucumber), Glycerin, Isopropanol, Meadowfoam Amidopropyl Betaine, Panthenol, PEG-10 Dimethicone, Water/Eau/Aqua

Questions?

1-888-346-4652

Distributed in the U.S. by Kimberly-Clark Global Sales, LLC, Roswell, GA 30076-2199

Distributed in Canada by Kimberly-Clark Inc., Mississauga, Ontario L5B 3Y5.

PRINCIPAL DISPLAY PANEL - 1L Bottle Label

34700

Kleenex®
BRAND MARQUE
ULTRA

Moisturizing Foam
Hand Sanitizer

SAME GREAT FORMULATION.
Now Kleenex® Branded

For Personal / Domestic Use Only

1L (33.8 fl oz)

Empty &
Discard Pump
PLASTIC
BOTTLE

how2recycle.info

NPN 80030706

ECOLOGO
PRODUCT CERTIFIED FOR
REDUCED ENVIRONMENTAL
IMPACT. VIEW SPECIFIC
ATTRIBUTES EVAUATED:
UL.COM/EL UL 2784

20-14-833-0-00